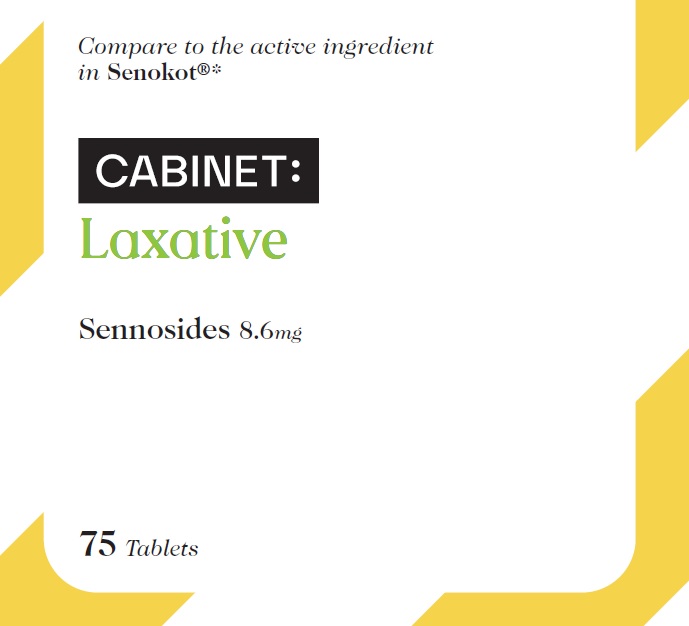 DRUG LABEL: VALUMEDS  NATURAL LAXATIVE
NDC: 68210-4101 | Form: TABLET, FILM COATED
Manufacturer: Spirit Pharmaceuticals LLC
Category: otc | Type: HUMAN OTC DRUG LABEL
Date: 20241210

ACTIVE INGREDIENTS: SENNOSIDES 8.6 mg/1 1
INACTIVE INGREDIENTS: SILICON DIOXIDE; CROSCARMELLOSE SODIUM; ANHYDROUS DIBASIC CALCIUM PHOSPHATE; HYPROMELLOSE, UNSPECIFIED; MINERAL OIL; MAGNESIUM STEARATE; CELLULOSE, MICROCRYSTALLINE; MALTODEXTRIN; WATER; SODIUM LAURYL SULFATE; STEARIC ACID

Sennosides 8.6mg

Drug Facts

Active ingredient (in each tablet)

Sennosides 8.6 mg

Purpose

Laxative

Uses

- relieves occasional constipation (irregularity)
- generally produces bowel movement in 6-12 hours

Warnings

Do not use

- laxative products for longer than 1 week, unless directed by a doctor

Ask a doctor before use if you have

- stomach pain
- nausea
- vomiting
- noticed a sudden change in bowel habits that lasts over 2 weeks

Stop use and ask a doctor if you have rectal bleeding or fail to have a bowel movement after use of a laxative. These may indicate a serious condition.

PREGNANCY OR BREAST FEEDING

If pregnant or breast-feeding, ask a health professional before use.

Keep out of reach of children. In case of overdose, get medical help or contact a Poison Control Center right away. (1800-222-1222)

Directions

- take preferably at bedtime or as directed by a doctor

Age | Starting Dosage | Maximum Dosage
adults and children 12 years of age or over | 2 tablets once a day | 4 tablets twice a day
children 6 to under 12 years | 1 tablet once a day | 2 tablets twice a day
children 2 to under 6 years | 1/2 tablet once a day | 1 tablet twice a day
children under 2 years | ask a doctor | ask a doctor

Other information

- each tablet contains: calcium 24 mg and sodium 3 mg
- store at 25°C (77°F); excursions permitted between 15°-30°C (59°-86°F)

Inactive ingredients

Colloidal silicon dioxide, croscarmellose sodium, dicalcium phosphate, hypromellose, liquid paraffin, magnesium stearate, microcrystalline cellulose, maltodextrin, purified water, sodium lauryl sulphate, stearic acid

Questions or comments?

1-888-333-9792

PDP

Cabinet:

Laxative

Sennosides 8.6mg

75 Tablets